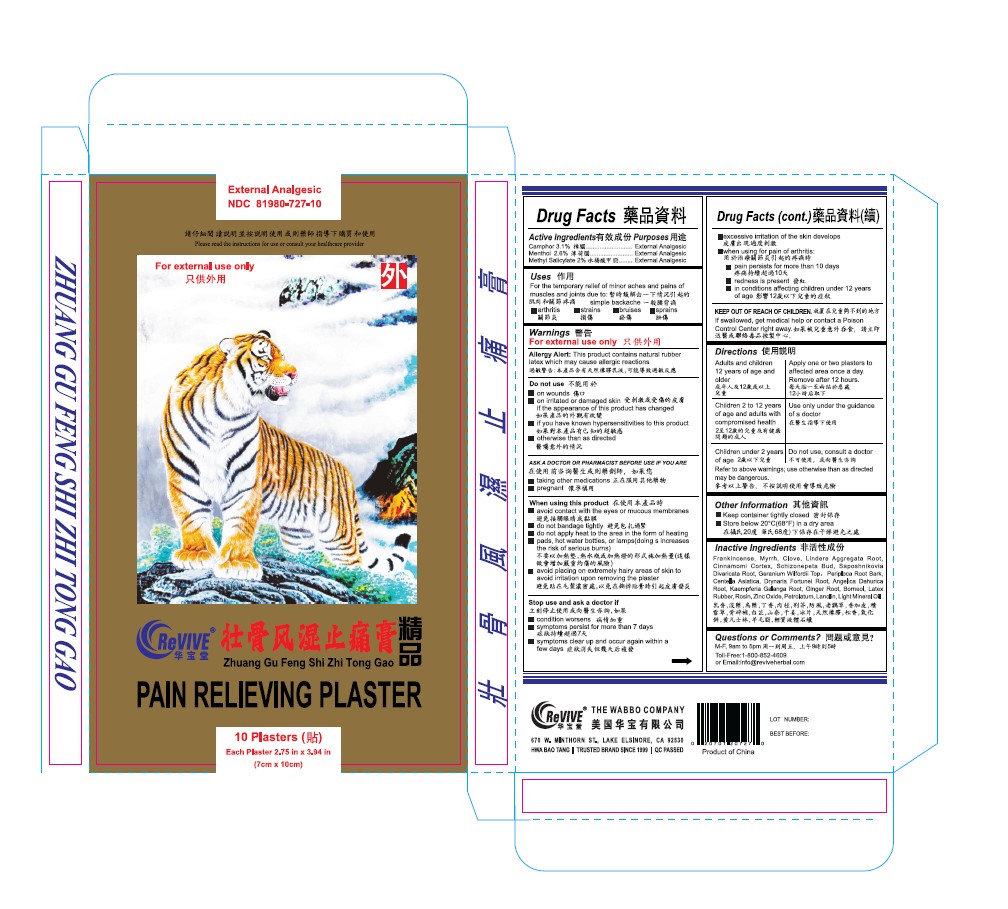 DRUG LABEL: Pain Relieving Plaster
NDC: 81980-727 | Form: PLASTER
Manufacturer: Health Body World Supply Inc.
Category: otc | Type: HUMAN OTC DRUG LABEL
Date: 20240703

ACTIVE INGREDIENTS: CAMPHOR (SYNTHETIC) 3.1 g/100 g; MENTHOL 2.6 g/100 g; METHYL SALICYLATE 2 g/100 g
INACTIVE INGREDIENTS: KAEMPFERIA GALANGA ROOT; NEPETA TENUIFOLIA FLOWERING TOP; DRYNARIA FORTUNEI ROOT; PERIPLOCA SEPIUM ROOT BARK; FRANKINCENSE; CENTELLA ASIATICA; BORNEOL; ROSIN; PETROLATUM; SAPOSHNIKOVIA DIVARICATA ROOT; GERANIUM WILFORDII TOP; GINGER; CLOVE; MYRRH; LINDERA AGGREGATA ROOT; CHINESE CINNAMON; LANOLIN; ZINC OXIDE; ANGELICA DAHURICA ROOT; LIGHT MINERAL OIL

Active ingredients

Camphor 3.1%

Menthol 2.6%

Methyl Salicylate 2%

Purposes

External Analgesic

Uses

For the temporary relief of minor aches and pains of muscles and joints due to

- simple backache
- arthritis
- strains
- bruises
- sprains

Warnings

For external use only

Allergy alert: this product contains natural rubber latex which may cause allergic reactions

Do not use

- on wounds
- on irritated or damaged skin if the appearance of this product has changed
- if you have known hypersensitivities to this product
- otherwise than as directed

Ask a doctor or pharmacist before use if you are

- taking other medications
- pregnant

when using this product

- avoid contact with the eyes or mucous membranes
- do not bandage tightly
- do not apply heat to the area in the form of heating
- pads, hot water bottles, or lamps (the risk of serious burns)
- avoid placing on extremely hairy areas of skin to avoid irritation upon removing the plaster

Stop use and ask a doctor if

- condition worsens
- symptoms persist for more than 7 days
- symptoms clear up and occur again within a few days
- excessive irritation of the skin develops
- when using for pain of arthritis:

- pain persists for more than 10 days

- redness is present

- in conditions affecting children under 12 years of age

Keep out of reach of children

If swallowed, get medical help or contact a Poison Control Center right away.

Directions

Adults and children 12 years of age and older

- Apply one or two plasters to affected area once a day. Remove after 12 hours.

Children 2 to 12 years of age and adults with compromised health

- Use only under the guidance of a doctor

Children under 2 years of age

Do not use, consult a doctor

Inactive ingredients

Frankincense, Myrrh, Clove, Lindera Aggregata Root, Cinnamomi Cortex, Schizonepeta Bud, Saposhnikovia Divaricata Root, Geranium Wilfordii Top, Periploca Root Bark, Centella Asiatica, Drynaria Fortunei Root, Angelica Dahurica Root, Kaempferia Galanga Root, Ginger Root, Borneol, Latex Rubber, Rosin, Zinc Oxide, Petrolatum, Lanolin, Light Mineral Oil